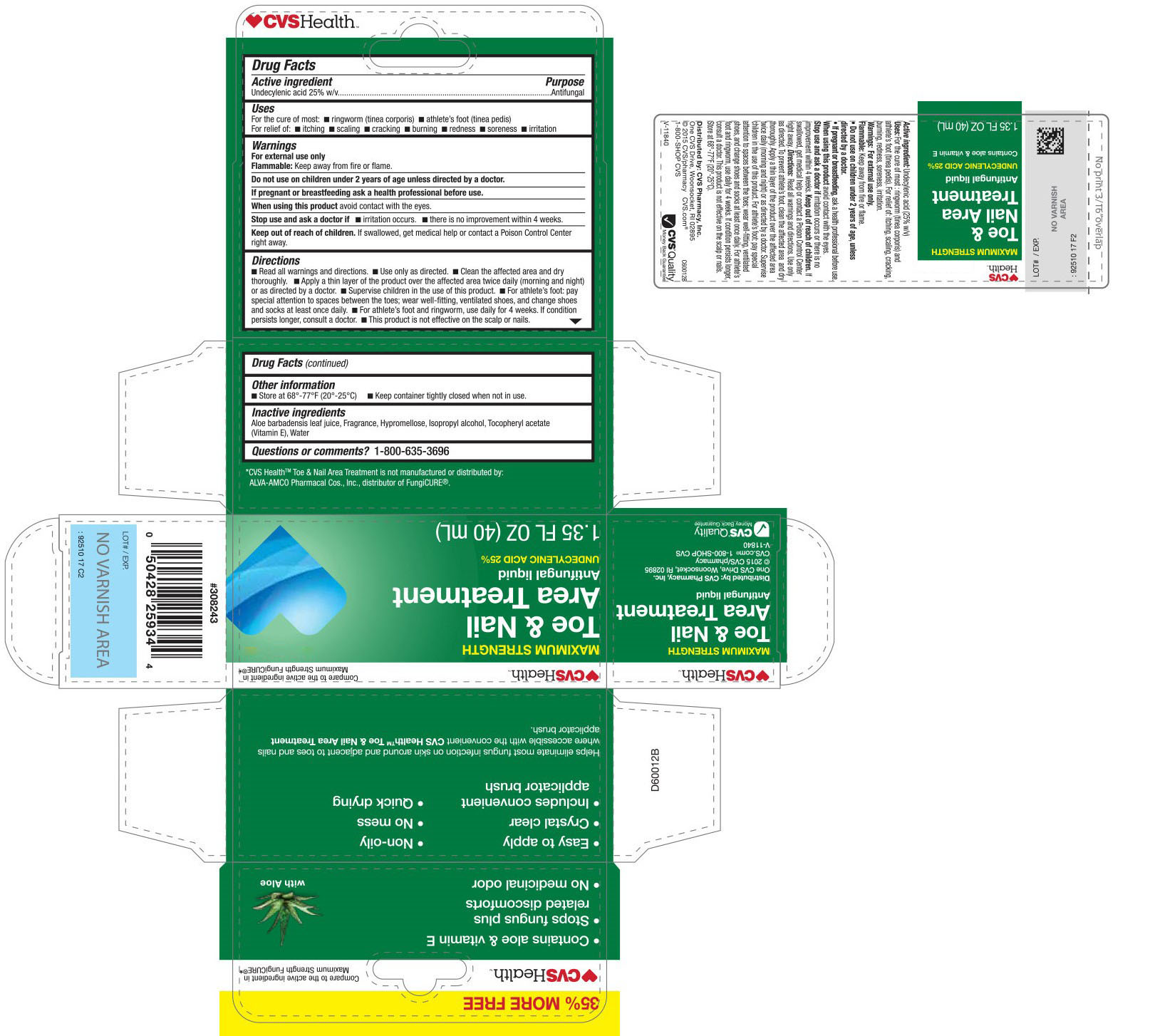 DRUG LABEL: CVS Pharmacy
NDC: 69842-718 | Form: LIQUID
Manufacturer: CVS Pharmacy
Category: otc | Type: HUMAN OTC DRUG LABEL
Date: 20170111

ACTIVE INGREDIENTS: UNDECYLENIC ACID 0.25 g/1 L
INACTIVE INGREDIENTS: ALOE VERA LEAF; HYPROMELLOSES; ISOPROPYL ALCOHOL; .ALPHA.-TOCOPHEROL ACETATE; WATER

Drug Facts

Drug Facts

Active Ingredient
Undecylenic acid 25% w/v

Purpose

Antifungal

Uses

For the cure of:

- ringworm (tinea corporis)
- athlete's foot (tinea pedis)

For the relief of:

- itching
- scaling
- cracking
- burning
- redness
- soreness
- irritation

Warnings

For external use only

Flammable:Keep away from fire or flame.

Do not use on children under 2 years of age unless directed by a doctor.

PREGNANCY OR BREAST FEEDING

If pregnant or breastfeeding ask a health professional before use.

When using this product

avoid contact with the eyes.

Stop use and ask a doctor if

- irritation occurs.
- there is no improvement within 4 weeks.

Keep out of reach of children.

If swallowed, get medical help or contact a poison control center right away.

Directions

- Read all warnings and directions.
- Use only as directed.
- Clean the affected area and dry thoroughly.
- Apply a thin layer of product over the affected area twice daily (morning and night) or as directed by a doctor.
- Supervise children in the use of this product.
- For athlete's foot: pay special attention to spaces between the toes; wear well-fitting, ventilated shoes, and change shoes and socks at least once daily.
- For athlete's foot and ringworm, use daily for 4 weeks. If condition persists longer, consult a doctor.
- This product is not effective on the scalp or nails.

Other information

- Store at 20o-25oC (68o-77oF)
- Keep container tightly closed when not in use.

Inactive ingredients

Aloe barbadensis leaf juice, Fragrance, Hypromellose, Isopropyl alcohol, Tocopheryl acetate (Vitamin E), Water